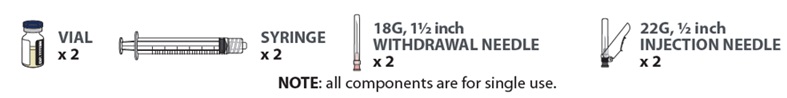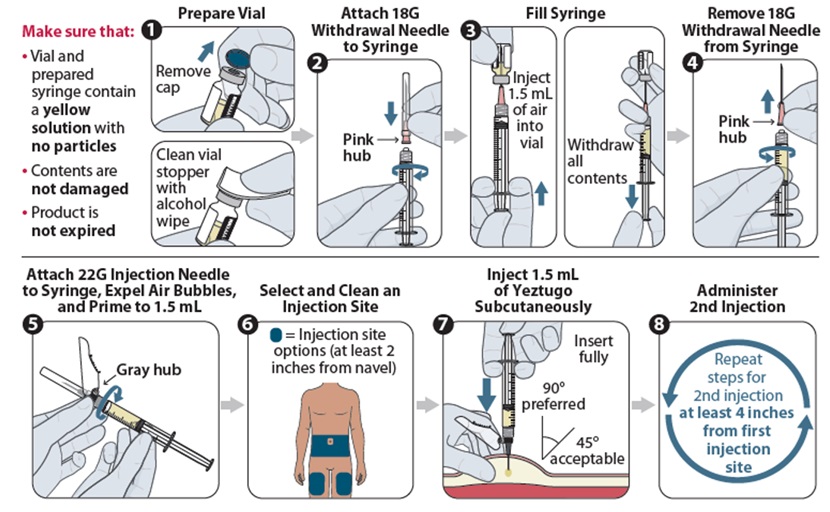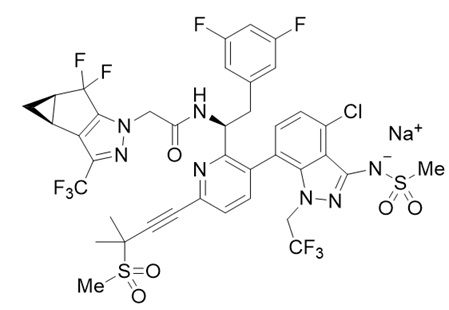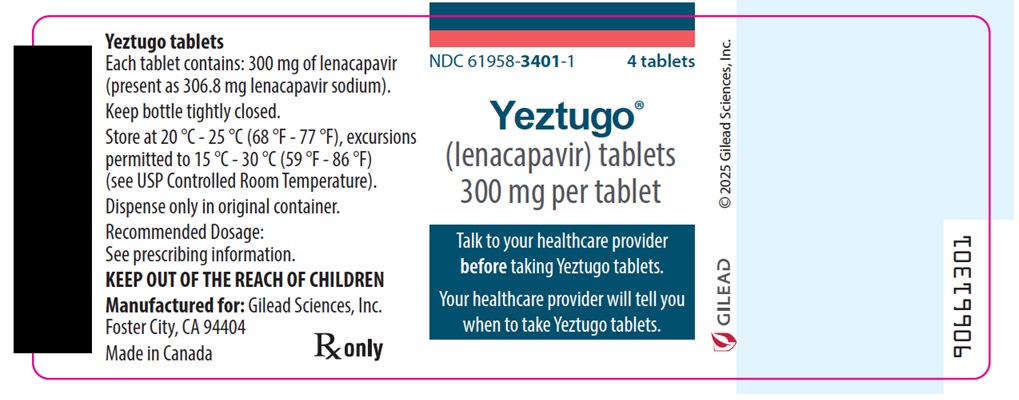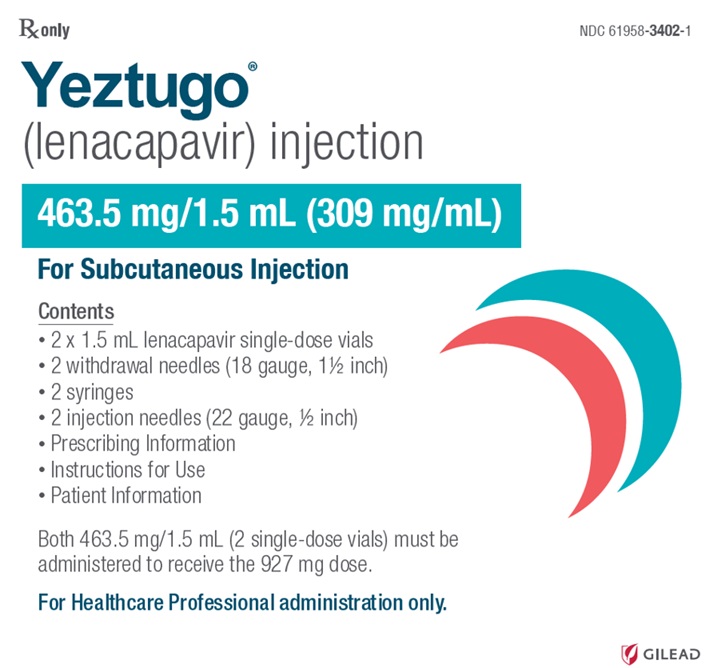 DRUG LABEL: Yeztugo
NDC: 61958-3401 | Form: TABLET, FILM COATED
Manufacturer: Gilead Sciences, Inc.
Category: prescription | Type: HUMAN PRESCRIPTION DRUG LABEL
Date: 20260212

ACTIVE INGREDIENTS: LENACAPAVIR SODIUM 300 mg/1 1
INACTIVE INGREDIENTS: COPOVIDONE K25-31; POLOXAMER 407; METHYL ALCOHOL; MANNITOL; MICROCRYSTALLINE CELLULOSE; CROSCARMELLOSE SODIUM; MAGNESIUM STEARATE

HIGHLIGHTS OF PRESCRIBING INFORMATION

These highlights do not include all the information needed to use YEZTUGO safely and effectively. See full prescribing information for YEZTUGO.
YEZTUGO® (lenacapavir) tablets, for oral use
YEZTUGO® (lenacapavir) injection, for subcutaneous use
Initial U.S. Approval: 2022

BOXED WARNING

WARNING: RISK OF DRUG RESISTANCE WITH USE OF YEZTUGO FOR HIV-1 PRE-EXPOSURE PROPHYLAXIS (PrEP) IN UNDIAGNOSED HIV-1 INFECTION

See full prescribing information for complete boxed warning.

Individuals must be tested for HIV-1 infection prior to initiating YEZTUGO, and with each subsequent injection of YEZTUGO, using a test approved or cleared by the FDA for the diagnosis of acute or primary HIV-1 infection. Drug-resistant HIV-1 variants have been identified with use of YEZTUGO by individuals with undiagnosed HIV-1 infection. Do not initiate YEZTUGO unless negative infection status is confirmed. Individuals who acquire HIV-1 while receiving YEZTUGO must transition to a complete HIV-1 treatment regimen (2.1, 4, 5.1, 5.2).

1 INDICATIONS AND USAGE

YEZTUGO, a human immunodeficiency virus type 1 (HIV-1) capsid inhibitor, is indicated for pre‑exposure prophylaxis (PrEP) to reduce the risk of sexually acquired HIV-1 in adults and adolescents weighing at least 35 kg who are at risk for HIV-1 acquisition. Individuals must have a negative HIV-1 test prior to initiating YEZTUGO. (1)

2 DOSAGE AND ADMINISTRATION

- HIV-1 screening: Screen all individuals for HIV-1 infection prior to initiating YEZTUGO, prior to each injection of YEZTUGO, and additionally as clinically appropriate. (2.1)
- Dosing schedule: Initiation dosing (injection and tablets) followed by once every 6-months continuation injection dosing. Tablets may be taken without regard to food. (2.3)

Initiation

Day 1

927 mg by subcutaneous injection (2 x 1.5 mL injections)
and
600 mg orally (2 x 300 mg tablets)

Day 2

600 mg orally (2 x 300 mg tablets)

Continuation

927 mg by subcutaneous injection (2 x 1.5 mL injections) every 6-months (26 weeks) from the date of the last injection +/-2 weeks.

- Anticipated delayed injections: If scheduled injection is anticipated to be delayed by more than 2 weeks, YEZTUGO tablets may be used on an interim basis (for up to 6 months if needed) until injections resume. Dosing schedule for delayed injection is 300 mg orally once every 7 days. (2.4)
- Missed injections: If more than 28 weeks have elapsed since the last injection and tablets have not been taken, restart initiation from Day 1 if clinically appropriate. (2.4)
- Dosage modifications (supplemental doses) of YEZTUGO are recommended when initiating strong or moderate CYP3A inducers. (2.5)
- YEZTUGO injection is for subcutaneous administration only. Two 1.5 mL injections are required for complete dose. (2.6)

3 DOSAGE FORMS AND STRENGTHS

Tablets: 300 mg of lenacapavir

Injection: 463.5 mg/1.5 mL (309 mg/mL) of lenacapavir in single-dose vials. (3)

4 CONTRAINDICATIONS

- Unknown or positive HIV-1 status. (4)

5 WARNINGS AND PRECAUTIONS

- Comprehensive management to reduce the risk of HIV-1 acquisition. (5.1)
- Potential risk of developing resistance to lenacapavir if an individual acquires HIV-1 either before or when receiving YEZTUGO, or following discontinuation of YEZTUGO. Test before each injection and additionally as clinically appropriate to confirm HIV-1 negative status (5.2)
- Residual concentrations of lenacapavir may remain in systemic circulation for up to 12 months or longer. (5.3)
- Improper administration (intradermal injection) has been associated with serious injection site reactions. (5.4)

6 ADVERSE REACTIONS

Most common adverse reactions (incidence greater than or equal to 5%, all grades) are injection site reactions, headache, and nausea. (6.1)

To report SUSPECTED ADVERSE REACTIONS, contact Gilead Sciences, Inc. at 1-800-GILEAD-5 or FDA at 1-800-FDA-1088 or www.fda.gov/medwatch.

7 DRUG INTERACTIONS

- Consult the Full Prescribing Information for important drug interactions with YEZTUGO. (7, 12.3)

FULL PRESCRIBING INFORMATION

BOXED WARNING

WARNING: RISK OF DRUG RESISTANCE WITH USE OF YEZTUGO FOR HIV-1 PRE-EXPOSURE PROPHYLAXIS (PrEP) IN UNDIAGNOSED HIV-1 INFECTION

Individuals must be tested for HIV-1 infection prior to initiating YEZTUGO, and with each subsequent injection of YEZTUGO, using a test approved or cleared by the FDA for the diagnosis of acute or primary HIV-1 infection. Drug-resistant HIV-1 variants have been identified with use of YEZTUGO by individuals with undiagnosed HIV-1 infection. Do not initiate YEZTUGO unless negative infection status is confirmed. Individuals who acquire HIV-1 while receiving YEZTUGO must transition to a complete HIV-1 treatment regimen [see Dosage and Administration (2.1), Contraindications (4), Warnings and Precautions (5.1, 5.2)].

1 INDICATIONS AND USAGE

YEZTUGO is indicated for pre‑exposure prophylaxis (PrEP) to reduce the risk of sexually acquired HIV-1 in adults and adolescents weighing at least 35 kg who are at risk for HIV-1 acquisition. Individuals must have a negative HIV-1 test prior to initiating YEZTUGO [see Dosage and Administration (2.1) and Warnings and Precautions (5.1)].

2 DOSAGE AND ADMINISTRATION

2.1 HIV-1 Screening for Individuals Receiving YEZTUGO for HIV-1 Pre-Exposure Prophylaxis

Screen all individuals for HIV-1 infection prior to initiating YEZTUGO, prior to each subsequent injection of YEZTUGO, and additionally as clinically appropriate, using a test approved or cleared by the FDA for the diagnosis of acute or primary HIV-1 infection. When screening for HIV-1 infection prior to initiating YEZTUGO, if an antigen/antibody-specific test is used and provides negative results, then such negative results should be confirmed using an RNA-specific assay, even if the results of the RNA-assay are available after YEZTUGO initiation. When screening for HIV-1 infection prior to continuing YEZTUGO, negative results from a rapid, point-of-care antigen/antibody test should be confirmed using a more sensitive assay [see Indications and Usage (1), Contraindications (4), Warnings and Precautions (5.1, 5.2) and Clinical Studies (14)].

2.2 Adherence to YEZTUGO

Prior to starting YEZTUGO, healthcare providers should select individuals who agree to the required testing and every 6 month injection dosing schedule, and counsel individuals about the importance of adherence to scheduled YEZTUGO dosing visits to help reduce the risk of acquiring HIV-1 infection and development of resistance [see Dosage and Administration (2.1), Warnings and Precautions (5.1, 5.2), and Microbiology (12.4)].

2.3 Recommended Dosage

The YEZTUGO dosing schedule in adults and adolescents weighing at least 35 kg consists of a required initiation dosing (subcutaneous injections and oral tablets) followed by once every 6-months continuation dosing (subcutaneous injections) (Table 1). YEZTUGO oral tablets may be taken with or without food [see Clinical Pharmacology (12.3)].

Table 1. Dosing Schedule for YEZTUGO Initiation and Continuation in Adults and Adolescents Weighing at Least 35 kg
Time
 | Dosage of YEZTUGO: Initiation [The complete initiation dosing schedule, consisting of subcutaneous injections and oral tablets, is required; the efficacy of YEZTUGO has only been established with this dosing schedule.]
Day 1 | 927 mg by subcutaneous injection (2 x 1.5 mL injections) and 600 mg orally (2 x 300 mg tablets)
Day 2 | 600 mg orally (2 x 300 mg tablets)
 | Dosage of YEZTUGO: Continuation
Every 6-months (26 weeks) [From the date of the last injection.] +/-2 weeks | 927 mg by subcutaneous injection (2 x 1.5 mL injections)

2.4 Dosing Schedule for Missed Dose

Missed Oral Initiation Dose

If the Day 2 oral initiation dose (600 mg; see Table 1) is missed, take it as soon as possible. Do not take Day 1 and Day 2 oral initiation doses on the same day.

Anticipated Delayed Injections

During continuation dosing, if the scheduled 6-month injection is anticipated to be delayed by more than 2 weeks, YEZTUGO tablets may be taken on an interim basis (for up to 6 months if needed), until injections resume. Refer to Table 2 below for the dosing schedule for delayed injections.

Table 2. Dosing Schedule for Anticipated Delayed Injections: Weekly Oral Dosage
Time since Last Injection | Dosage of YEZTUGO
26 to 28 weeks | Oral dosage of 300 mg taken once every 7 days. [Use on an interim basis only (for up to 6 months if needed).]
 | Resume the continuation injection dosage within 7 days after the last oral dose.

Missed Injections

Individuals who miss a scheduled injection visit should be clinically reassessed to ensure resumption of YEZTUGO remains appropriate and that the individual remains HIV-1 negative. During continuation dosing, if more than 28 weeks have elapsed since the last injection and YEZTUGO tablets have not been taken, see Table 3 below for the dosing schedule after missed injections. Adherence to the injection dosing schedule is strongly recommended [see Dosage and Administration (2.2) and Microbiology (12.4)].

Table 3. Dosing Schedule after Missed Injections
Time since Last Injection | Dosage of YEZTUGO
More than 28 weeks | Reinitiate with initiation dosing schedule from Day 1 (Table 1) and then continue with continuation injection dosing.

2.5 Dosage Modifications for Co-administration with Strong or Moderate CYP3A Inducers

Supplemental doses of YEZTUGO are recommended for individuals initiating therapy with either strong CYP3A inducers (see Table 4) or moderate CYP3A inducers (see Table 5) [see Drug Interactions (7.1) and Clinical Pharmacology (12.3)].

Strong CYP3A inducers may be initiated starting at least 2 days after YEZTUGO is first initiated, while moderate CYP3A inducers may be started any time after YEZTUGO is first initiated.

Table 4. Dosing Recommendations for Individuals Receiving YEZTUGO and Initiating Therapy with Strong CYP3A Inducers [Dosing recommendations are not available for the initiation of YEZTUGO in individuals already receiving strong CYP3A inducers, nor in individuals receiving the weekly oral dosage of YEZTUGO (see Table 2).]
Maintain Scheduled Continuation Injection Dosing | Schedule for Supplemental Doses of YEZTUGO
Maintain Scheduled Continuation Injection Dosing | Time | Dosage
Continue to administer once every 6-months scheduled continuation dosing of YEZTUGO 927 mg subcutaneously (2 x 1.5 mL injections) (see Table 1), plus administer supplemental doses of YEZTUGO as shown in this table | On day strong CYP3A inducer is initiated (which should be at least 2 days after YEZTUGO is first initiated) | Supplemental dosage: Step 1 927 mg subcutaneously (2 x 1.5 mL injections) and 600 mg orally (2 x 300 mg tablets)
Continue to administer once every 6-months scheduled continuation dosing of YEZTUGO 927 mg subcutaneously (2 x 1.5 mL injections) (see Table 1), plus administer supplemental doses of YEZTUGO as shown in this table | On day after strong CYP3A inducer is initiated | Supplemental dosage: Step 2 600 mg orally (2 x 300 mg tablets)
Continue to administer once every 6-months scheduled continuation dosing of YEZTUGO 927 mg subcutaneously (2 x 1.5 mL injections) (see Table 1), plus administer supplemental doses of YEZTUGO as shown in this table | If strong CYP3A inducer is co-administered for longer than 6 months | Subsequent supplemental dosage Every 6-months [26 weeks +/-2 weeks.] from initiation of strong CYP3A inducer, continue to administer supplemental doses of YEZTUGO as described above in Steps 1 and 2.
Continue to administer once every 6-months scheduled continuation dosing of YEZTUGO 927 mg subcutaneously (2 x 1.5 mL injections) (see Table 1), plus administer supplemental doses of YEZTUGO as shown in this table | After stopping the strong CYP3A inducer, continue the once every 6-months scheduled continuation injection dosing of YEZTUGO (see Table 1).

Table 5. Dosing Recommendations for Individuals Receiving YEZTUGO and Initiating Therapy with Moderate CYP3A Inducers [Dosing recommendations are not available for the initiation of YEZTUGO in individuals already receiving moderate CYP3A inducers, nor in individuals receiving the weekly oral dosage of YEZTUGO (see Table 2).]
Maintain Scheduled Continuation Injection Dosing | Schedule for Supplemental Doses of YEZTUGO
Maintain Scheduled Continuation Injection Dosing | Time | Dosage
Continue to administer once every 6-months scheduled continuation dosing of YEZTUGO 927 mg subcutaneously (2 x 1.5 mL injections) (see Table 1), plus administer supplemental doses of YEZTUGO as shown in this table | On day moderate CYP3A inducer is initiated | Supplemental dosage 463.5 mg subcutaneously (1 x 1.5 mL injection)
Continue to administer once every 6-months scheduled continuation dosing of YEZTUGO 927 mg subcutaneously (2 x 1.5 mL injections) (see Table 1), plus administer supplemental doses of YEZTUGO as shown in this table | If moderate CYP3A inducer is co-administered for longer than 6 months | Subsequent supplemental dosage Every 6-months [26 weeks +/-2 weeks.] from initiation of moderate CYP3A inducer, continue to administer a supplemental dose of YEZTUGO as described above.
Continue to administer once every 6-months scheduled continuation dosing of YEZTUGO 927 mg subcutaneously (2 x 1.5 mL injections) (see Table 1), plus administer supplemental doses of YEZTUGO as shown in this table | After stopping the moderate CYP3A inducer, continue the once every 6-months scheduled continuation injection dosing of YEZTUGO (see Table 1).

2.6 Preparation and Administration of Subcutaneous Injection

YEZTUGO injection is only for subcutaneous administration into the abdomen by a healthcare provider. The thigh can be used as an alternative injection site if preferred. Do NOT administer intradermally due to risk of serious injection site reactions [see Warnings and Precautions (5.4)].

Use aseptic technique. Visually inspect the solution in the vials and prepared syringe for particulate matter and discoloration prior to administration. YEZTUGO injection is a yellow solution. Do not use YEZTUGO injection if the solution is discolored or if it contains particulate matter. Once the solution is withdrawn from the vials, the subcutaneous injections should be administered as soon as possible [see How Supplied/Storage and Handling (16)].

Figure 1 identifies the components for use in the administration steps for the withdrawal needle injection kit, and the administration steps are provided in Figure 2. The 18-gauge needle is for withdrawal only in this kit.

The injection kit components are for single use only. Two 1.5 mL injections are required for a complete dose.

Figure 1 YEZTUGO Withdrawal Needle Injection Kit Components

Figure 2 YEZTUGO Injection Steps for Withdrawal Needle Injection Kit

3 DOSAGE FORMS AND STRENGTHS

YEZTUGO tablets: Each tablet contains 300 mg of lenacapavir (present as 306.8 mg of lenacapavir sodium). The tablets are beige, capsule-shaped, film-coated, and debossed with ‘GSI’ on one side of the tablet and ‘62L’ on the other side of the tablet.

YEZTUGO injection: Each single-dose vial contains 463.5 mg/1.5 mL (309 mg/mL) of lenacapavir (present as 473.1 mg/1.5 mL of lenacapavir sodium). The lenacapavir injectable solution is sterile, preservative-free, clear, and yellow with no visible particles.

4 CONTRAINDICATIONS

YEZTUGO is contraindicated in individuals with unknown or positive HIV-1 status [see Warnings and Precautions (5.1)].

5 WARNINGS AND PRECAUTIONS

5.1 Comprehensive Management to Reduce the Risk of HIV-1 Infection and Other Sexually Acquired Infections

Use YEZTUGO to reduce the risk of HIV-1 acquisition as part of a comprehensive prevention strategy including adherence to the administration schedule and safer sex practices, including condoms, to reduce the risk of sexually transmitted infections (STIs). YEZTUGO is not always effective in preventing HIV-1 acquisition [see Clinical Studies (14)]. The time from initiation of YEZTUGO for HIV-1 PrEP to maximal protection against HIV-1 infection is unknown.

Risk for HIV-1 acquisition includes behavioral, biological, or epidemiologic factors including, but not limited to, condomless sex, past or current STIs, self-identified HIV risk, having sexual partners of unknown HIV-1 viremic status, or sexual activity in a high prevalence area or network.

Counsel individuals on the use of other prevention measures (e.g., consistent and correct condom use; knowledge of partner(s)’ HIV-1 status, including viral suppression status; regular testing for STIs that can facilitate HIV-1 transmission). Inform individuals about and support their efforts in reducing sexual behaviors associated with HIV-1 acquisition risk.

Use YEZTUGO to reduce the risk of HIV-1 acquisition only in individuals confirmed to be HIV-1 negative [see Contraindications (4)]. Evaluate for current or recent signs or symptoms consistent with acute HIV-1 infection (e.g., fever, fatigue, myalgia, skin rash). Confirm HIV-1 negative status prior to initiating YEZTUGO, prior to each subsequent injection of YEZTUGO, and additionally as clinically appropriate (e.g., upon diagnosis of other sexually transmitted infections or if clinical symptoms consistent with acute HIV-1 infection are present) using a test approved or cleared by the FDA for the diagnosis of acute or primary HIV-1 infection [see Dosage and Administration (2.1)].

Counsel and support individuals on adhering to the YEZTUGO administration schedule, on the use of other measures to reduce the risk of STIs, and on the importance of routine testing for HIV-1 and other STIs. Some individuals, such as adolescents, may benefit from additional counseling and appointment reminders to support adherence to the dosing and testing schedule [see Use in Specific Populations (8.4)].

5.2 Potential Risk of Resistance with YEZTUGO

There is a potential risk of developing resistance to YEZTUGO if an individual acquires HIV-1 either before or when receiving YEZTUGO, or following discontinuation of YEZTUGO. HIV-1 resistance substitutions may emerge in individuals with undiagnosed HIV-1 infection who are taking only YEZTUGO, because YEZTUGO alone does not constitute a complete regimen for HIV-1 treatment [see Microbiology (12.4)].

To minimize this risk, it is essential to test before each injection and additionally as clinically appropriate (e.g., upon diagnosis of other sexually transmitted infections or if clinical symptoms consistent with acute HIV-1 infection are present) to confirm HIV-1 negative status using a test approved or cleared by the FDA for the diagnosis of acute or primary HIV-1 infection. Individuals who are confirmed to have HIV-1 must immediately begin a complete HIV-1 treatment regimen to reduce the risk of developing resistance.

In addition, due to the long-acting properties of YEZTUGO, alternative forms of PrEP should be considered following discontinuation of YEZTUGO for those individuals with HIV-1 negative status who are at continuing risk of HIV-1 acquisition and initiated within 28 weeks of the last YEZTUGO injection [see Warnings and Precautions (5.3)].

5.3 Long-Acting Properties and Potential Associated Risks with YEZTUGO

Healthcare providers should take the long-acting properties of YEZTUGO into consideration when YEZTUGO is prescribed. Residual concentrations of lenacapavir may remain in the systemic circulation of individuals for prolonged periods (up to 12 months or longer after the last subcutaneous dose).

It is important to select individuals who agree to the required injection dosing schedule because non-adherence to every-6-monthly injections or missed doses could lead to HIV-1 acquisition and development of resistance.

Lenacapavir, a moderate CYP3A inhibitor, may increase the exposure to, and therefore potential risk of adverse reactions from, drugs primarily metabolized by CYP3A initiated within 9 months after the last subcutaneous dose of YEZTUGO [see Drug Interactions (7.2) and Clinical Pharmacology (12.3)].

5.4 Serious Injection Site Reactions with Improper Administration

Improper administration (intradermal injection) of lenacapavir has been associated with serious injection site reactions, including necrosis and ulcer. Ensure YEZTUGO is only administered subcutaneously [see Dosage and Administration (2.6)].

6 ADVERSE REACTIONS

The following adverse reactions are discussed in other sections of the labeling:

- Serious Injection Site Reactions with Improper Administration [see Warnings and Precautions (5.4)].

6.1 Clinical Trials Experience

Because clinical trials are conducted under widely varying conditions, adverse reaction rates observed in the clinical trials of a drug cannot be directly compared to rates in the clinical trials of another drug and may not reflect the rates observed in practice.

The primary safety assessment of YEZTUGO is based on data from two randomized, double-blind, active-controlled trials, PURPOSE 1 and PURPOSE 2, in which a total of 8616 adult and adolescent participants received YEZTUGO (N=4323), DESCOVY (emtricitabine [FTC]/tenofovir alafenamide [TAF]; N=2135) once daily, or TRUVADA (FTC/tenofovir disoproxil fumarate [TDF]; N=2158) once daily for HIV-1 PrEP. In PURPOSE 1, the median duration of exposure to YEZTUGO, DESCOVY, and TRUVADA was 43, 42, and 41 weeks, respectively. In PURPOSE 2, the median duration of exposure to both YEZTUGO and TRUVADA was 39 weeks.

The most common adverse reactions (all Grades) reported in at least 5% of participants receiving YEZTUGO in either PURPOSE 1 or PURPOSE 2 were injection site reactions, headache, and nausea. In PURPOSE 1, <1% of participants in the groups receiving YEZTUGO, DESCOVY or TRUVADA, discontinued due to adverse events (all causality). In PURPOSE 2, 1% of participants in the group receiving YEZTUGO and <1% of participants receiving TRUVADA discontinued due to adverse events (all causality). Table 6 presents the frequency of adverse reactions (all Grades) in at least 2% of participants receiving YEZTUGO in either PURPOSE 1 or PURPOSE 2.

Table 6. Adverse Drug Reactions (All Grades) Reported in ≥2% [Frequencies of adverse reactions are based on all adverse events attributed to study drug (or to the procedure for injection site reactions) by the investigator.] of Participants Receiving YEZTUGO in PURPOSE 1 or PURPOSE 2
 | PURPOSE 1 |  | PURPOSE 2
Adverse Reaction | YEZTUGO N=2140 | TRUVADA [Participants received placebo subcutaneous injections (polyethylene glycol 400).] N=1070 | YEZTUGO N=2183 | TRUVADA N=1088
Injection Site Reactions | 69% | 34% | 83% | 69%
Headache | 7% | 8% | 2% | 2%
Nausea | 5% | 11% | 2% | 4%
Dizziness | 4% | 6% | <1% | 1%
Vomiting | 4% | 7% | <1% | 1%
Diarrhea | 4% | 4% | 2% | 2%

Injection-Associated Adverse Reactions

Local Injection Site Reactions (ISRs)

The most frequent adverse reactions associated with lenacapavir injection for subcutaneous use in PURPOSE 1 and PURPOSE 2 were ISRs. The most commonly reported ISRs (all grades) in at least 2% of participants who received YEZTUGO in either PURPOSE 1 or PURPOSE 2 are presented in Table 7.

PURPOSE 1

In PURPOSE 1, 69% of participants receiving YEZTUGO experienced ISRs, compared to 35% of participants receiving placebo injections (and DESCOVY or TRUVADA). Most participants who received YEZTUGO had mild (Grade 1, 50%) or moderate (Grade 2, 19%) severity ISRs. Grade 3 ISRs were reported in 4 (0.2%) participants, and included ulcer and nodule. YEZTUGO was discontinued due to ISRs in 4 (0.2%) participants. None of the ISRs were serious. The incidence of reported ISRs decreased with subsequent injections.

Nodules: Injection site nodule was reported in 64% of participants who received YEZTUGO and resolved more slowly than other ISRs. The median duration of nodules associated with the first injections of YEZTUGO was 350 (interquartile range: 182, 470) days. The median of the maximum observed nodule diameter from each participant was 3.0 (interquartile range: 2.0, 3.5) cm.

Other ISRs: The other ISRs reported in more than 2% of participants who received YEZTUGO were pain (31%), swelling (4%), induration (4%), and pruritus (2%). The median duration of induration, which resolved more slowly than most other ISRs, was 173 (interquartile range: 22, 267) days. The median duration of ISRs, excluding nodules and indurations, was 9 (interquartile range: 4 to 30) days.

PURPOSE 2

In PURPOSE 2, 83% of participants receiving YEZTUGO experienced ISRs, compared to 69% of participants receiving placebo injections (and TRUVADA). Most participants had mild (Grade 1, 66%) or moderate (Grade 2, 17%) severity ISRs. Grade 3 ISRs were reported in 14 (0.6%) participants, and included ulcer, pain, erythema, edema, and dermatitis. YEZTUGO was discontinued due to ISRs in 26 (1.2%) participants. None of the ISRs were serious. The incidence of reported ISRs decreased with subsequent injections.

Nodules: Injection site nodule was reported in 63% of participants who received YEZTUGO and resolved more slowly than other ISRs. The median duration of nodules associated with the first injections of YEZTUGO was 297 (interquartile range: 176, 423) days. The median of the maximum observed nodule diameter for each participant was 3.0 (interquartile range: 2.0, 4.0) cm.

Other ISRs: The other ISRs reported in more than 2% of participants who received YEZTUGO were pain (56%), erythema (17%), induration (16%), swelling (7%), bruising (3%), pruritus (3%), and warmth (2%). The median duration of induration, which resolved more slowly than most other ISRs, was 151 (interquartile range: 15, 267) days. The median duration of ISRs, excluding nodules and indurations, was 4 (interquartile range: 2 to 8) days.

Table 7. Injection Site Reactions (All Grades) Reported in ≥2% [Frequencies are based on all injection site reactions attributed to study drug (or to the procedure) by the investigator.] of Participants Receiving YEZTUGO in PURPOSE 1 or PURPOSE 2
 | PURPOSE 1 |  | PURPOSE 2
Injection Site Reactions | YEZTUGO N=2140 | DESCOVY or TRUVADA [Participants received placebo subcutaneous injections (polyethylene glycol 400).] N=3205 | YEZTUGO N=2183 | TRUVADA N=1088
Nodule | 64% | 17% | 63% | 39%
Pain | 31% | 24% | 56% | 53%
Induration | 4% | <1% | 16% | 10%
Swelling | 4% | 5% | 7% | 10%
Pruritus | 2% | 1% | 3% | 3%
Erythema | 1% | 1% | 17% | 19%
Bruising | <1% | <1% | 3% | 4%
Warmth | <1% | <1% | 2% | 2%

Nodules and Indurations Dermatopathology

In a separate clinical trial (CAPELLA) in participants with HIV-1 who received lenacapavir via subcutaneous injection, skin biopsies of injection site nodules or indurations revealed dermatopathological findings of foreign body inflammation or granulomatous response in some participants.

7 DRUG INTERACTIONS

7.1 Effect of Other Drugs on YEZTUGO

Lenacapavir is a substrate of P-gp, UGT1A1, and CYP3A.

Strong or Moderate CYP3A Inducers

Drugs that are strong or moderate inducers of CYP3A may significantly decrease plasma concentrations of lenacapavir, which may reduce the effectiveness of YEZTUGO. Therefore, dosage modifications (supplemental doses) of YEZTUGO are recommended when initiating strong or moderate CYP3A inducers [see Dosage and Administration (2.5) and Clinical Pharmacology (12.3)].

Combined P-gp, UGT1A1, and Strong CYP3A Inhibitors

Combined P-gp, UGT1A1, and strong CYP3A inhibitors may significantly increase plasma concentrations of YEZTUGO. Concomitant administration of YEZTUGO with these inhibitors is not recommended.

7.2 Effect of YEZTUGO on Other Drugs

CYP3A and P-gp Substrates

Lenacapavir is a moderate inhibitor of CYP3A and a P-gp inhibitor.

The co-administration of YEZTUGO with sensitive substrates of CYP3A or P-gp may increase the concentrations of these substrates and result in the increased risk of their adverse events. See the prescribing information of these sensitive substrates for dosing recommendations or appropriate monitoring of safety.

Due to the long half-life of lenacapavir following subcutaneous administration, YEZTUGO may increase the exposure of drugs primarily metabolized by CYP3A [see Clinical Pharmacology (12.3)] initiated within 9 months after the last subcutaneous dose of YEZTUGO.

7.3 Drugs without Clinically Significant Interactions with YEZTUGO

Based on drug interaction studies conducted with YEZTUGO, no clinically significant drug interactions have been observed with: atorvastatin, famotidine, pitavastatin, rosuvastatin, tenofovir alafenamide, and voriconazole.

8 USE IN SPECIFIC POPULATIONS

8.1 Pregnancy

Pregnancy Exposure Registry

There is a pregnancy exposure registry that monitors pregnancy outcomes in individuals exposed to YEZTUGO during pregnancy. Healthcare providers are encouraged to register individuals by calling the Antiretroviral Pregnancy Registry (APR) at 1-800-258-4263.

Risk Summary

Available data from a randomized, controlled trial (PURPOSE 1) with YEZTUGO use during pregnancy have not identified a drug-associated risk for miscarriage, or adverse maternal or fetal outcomes when compared to the active control (see Data). The rate of major birth defects in YEZTUGO-exposed pregnancies did not exceed the background prevalence rates. The risk estimates are imprecise due to small numbers of exposed pregnancies (see Data). There is an increased risk of HIV-1 transmission from the mother to the child during acute HIV-1 infection (see Clinical Considerations). In animal reproduction studies, no adverse developmental effects were observed when lenacapavir was administered to rats and rabbits at exposures (AUC) ≥7 times the exposure in humans at the recommended human dose (RHD) of YEZTUGO (see Data).

The APR has been established to monitor for birth defects following prenatal exposure to antiretrovirals. The APR uses the Metropolitan Atlanta Congenital Defects Program (MACDP) as the U.S. reference population for birth defects in the general population. The background rate for major birth defects is 2.7% in the MACDP. The rate of miscarriage for individual drugs is not reported in the APR. In the U.S. general population, the estimated background risk of miscarriage in clinically recognized pregnancies is 15–20%. The MACDP evaluates mothers and infants from a limited geographic area and does not include outcomes for births that occurred at < 20 weeks gestation.

Clinical Considerations

Disease-associated maternal and/or embryo/fetal risk

Published studies indicate an increased risk of HIV-1 infection during pregnancy and an increased risk of mother to child transmission during acute HIV-1 infection. In women at risk of acquiring HIV-1, consideration should be given to methods to prevent acquisition of HIV-1, including continuing or initiating YEZTUGO for HIV-1 PrEP, during pregnancy.

Data

Human Data

In a randomized, controlled trial in Uganda and South Africa (PURPOSE 1), there were 208 pregnancies exposed to YEZTUGO with known outcomes and 132 deliveries (both live and non-live). In the active control arm of PURPOSE 1, there were 109 pregnancies exposed to TRUVADA with known outcomes and 61 deliveries (both live and non-live). The adverse pregnancy outcomes of spontaneous abortion, stillbirth, preterm birth, and small for gestational age were similar across both treatment groups.

There were two major birth defects in the YEZTUGO arm. Both were ventricular septal defects. This resulted in a rate of major birth defects that fell within the background prevalence rate for major birth defects.

Concentrations of YEZTUGO during each trimester of pregnancy and postpartum were comparable to those in non-pregnant participants [see Clinical Pharmacology (12.3)].

Animal Data

Lenacapavir was administered intravenously to pregnant rabbits (up to 20 mg/kg/day on gestation days (GD) 7 to 19), orally to rats (up to 300 mg/kg/day on GD 6 to 17), and subcutaneously to rats (up to 300 mg/kg on GD 6). No significant toxicological effects on embryo-fetal (rats and rabbits) or pre/postnatal (rats) development were observed at exposures (AUC) approximately 21 times (rats) and 170 times (rabbits) the exposure in humans at the RHD of YEZTUGO.

8.2 Lactation

Risk Summary

Lenacapavir is present in human milk. Lenacapavir was detected at very low levels in infants who were breastfed by individuals who became pregnant while receiving YEZTUGO (see Data). No adverse effects of lenacapavir in breastfed infants have been observed. It is not known if YEZTUGO affects milk production.

In women without HIV-1 infection, the developmental and health benefits of breastfeeding and the mother’s clinical need for YEZTUGO for HIV-1 PrEP should be considered along with any potential adverse effects on the breastfed child from YEZTUGO and the risk of HIV-1 acquisition due to nonadherence and subsequent mother to child transmission.

Data

Human Data

The median lenacapavir concentration in human breast milk to maternal plasma ratio in participants (n=8) who received YEZTUGO was 0.63 (range: 0.29 to 1.90). The median infant-to-mother plasma ratio for lenacapavir in infants (n=10) who were breastfed by individuals receiving YEZTUGO from 0 to less than 13 weeks after delivery was 0.06 (range: 0.01 to 0.20).

8.4 Pediatric Use

The safety and effectiveness of YEZTUGO for HIV-1 PrEP in adolescents weighing at least 35 kg who are at risk for HIV-1 acquisition is supported by 2 adequate and well-controlled trials, PURPOSE 1 and PURPOSE 2, that enrolled both adults and adolescents [see Adverse Reactions (6.1), Clinical Pharmacology (12.3), and Clinical Studies (14)].

PURPOSE 1 and PURPOSE 2 enrolled a total of 128 adolescent participants. In the 59 adolescents who received YEZTUGO, the safety data were comparable to the safety data reported in adults receiving YEZTUGO.

HIV-1 testing should be conducted prior to initiating YEZTUGO, prior to each subsequent injection of YEZTUGO, and additionally as clinically appropriate, using a test approved or cleared by the FDA for the diagnosis of acute or primary HIV-1 infection. Adolescents may benefit from additional counseling and appointment reminders to support adherence to the dosing and testing schedule [see Dosage and Administration (2.2), Warnings and Precautions (5.1)].

The safety, effectiveness, and pharmacokinetics of YEZTUGO in pediatric populations weighing less than 35 kg have not been established.

8.5 Geriatric Use

Clinical studies of YEZTUGO did not include sufficient numbers of participants aged 65 and over to determine whether they respond differently from younger individuals. In general, caution should be exercised in administration of YEZTUGO in elderly individuals, reflecting greater frequency of decreased hepatic, renal, or cardiac function and of concomitant disease or other drug therapy [see Clinical Pharmacology (12.3)].

8.6 Renal Impairment

No dosage adjustment of YEZTUGO is recommended in individuals with mild, moderate or severe renal impairment (estimated creatinine clearance greater than or equal to 15 mL per minute). YEZTUGO has not been studied in individuals with ESRD (estimated creatinine clearance less than 15 mL per minute) [see Clinical Pharmacology (12.3)].

8.7 Hepatic Impairment

No dosage adjustment of YEZTUGO is recommended in individuals with mild (Child-Pugh Class A) or moderate (Child-Pugh Class B) hepatic impairment. YEZTUGO has not been studied in individuals with severe hepatic impairment (Child-Pugh Class C) [see Clinical Pharmacology (12.3)].

10 OVERDOSAGE

No data are available on overdose of YEZTUGO. If overdose occurs, monitor the individual for evidence of toxicity. Treatment of overdose with YEZTUGO consists of general supportive measures including monitoring of vital signs as well as observation of the clinical status of the individual. As lenacapavir is highly bound to plasma proteins, it is unlikely to be significantly removed by dialysis.

11 DESCRIPTION

YEZTUGO tablets and YEZTUGO injection contain lenacapavir sodium, a capsid inhibitor.

The chemical name of lenacapavir sodium is: Sodium (4-chloro-7-(2-((S)-1-(2-((3bS,4aR)-5,5-difluoro-3-(trifluoromethyl)-3b,4,4a,5-tetrahydro-1H-cyclopropa[3,4]cyclopenta[1,2-c]pyrazol-1-yl)acetamido)-2-(3,5-difluorophenyl)ethyl)-6-(3-methyl-3-(methylsulfonyl)but-1-yn-1-yl)pyridin-3-yl)-1-(2,2,2-trifluoroethyl)-1H-indazol-3-yl)(methylsulfonyl)amide.

Lenacapavir sodium has a molecular formula of C39H31ClF10N7NaO5S2, a molecular weight of 990.3, and the following structural formula:

Lenacapavir sodium is a light yellow to yellow solid and is practically insoluble in water.

YEZTUGO tablets are for oral administration. Each film-coated tablet contains 300 mg of lenacapavir (present as 306.8 mg lenacapavir sodium) and the following inactive ingredients: copovidone, croscarmellose sodium, magnesium stearate, mannitol, microcrystalline cellulose, and poloxamer 407. The tablets are film-coated with a coating material containing iron oxide black, iron oxide red, iron oxide yellow, polyethylene glycol, polyvinyl alcohol, talc, and titanium dioxide.

YEZTUGO injection is for subcutaneous administration. Each single-dose vial contains 463.5 mg/1.5 mL (309 mg/mL) of lenacapavir (present as 473.1 mg/1.5 mL of lenacapavir sodium) as a sterile, preservative-free, clear, yellow solution and the following inactive ingredients: 896.3 mg of polyethylene glycol 300 (as solvent) and water for injection. The apparent pH range of the injection is 9.0-10.2.

The vial stoppers are not made with natural rubber latex.

12 CLINICAL PHARMACOLOGY

12.1 Mechanism of Action

YEZTUGO is an HIV-1 antiretroviral agent with long-acting properties [see Microbiology (12.4)].

12.2 Pharmacodynamics

Cardiac Electrophysiology

At supratherapeutic exposures of lenacapavir (16-fold higher than the therapeutic exposures of YEZTUGO), YEZTUGO does not prolong the QTcF interval to any clinically relevant extent.

12.3 Pharmacokinetics

The pharmacokinetic (PK) properties of lenacapavir are provided in Table 8. The population PK parameter estimates of YEZTUGO after oral and subcutaneous administration to adults are provided in Table 9. Similar exposures are achieved when YEZTUGO is administered subcutaneously in the abdomen or thigh.

Table 8. Pharmacokinetic Properties of Lenacapavir
 |  | Oral | Subcutaneous
Absorption
% Absolute bioavailability |  | 4 to 7 | 91 [Values reflect absolute bioavailability following subcutaneous administration of the 927 mg dose.]
Tmax [Values reflect administration of lenacapavir with or without food.] |  | 4 hours | 77 to 84 days [Subcutaneously administered lenacapavir forms a drug depot whereby lenacapavir is slowly released from the site of administration.]
Effect of Food
Effect of low-fat meal (relative to fasting) [Values refer to geometric mean ratio [low-fat meal/fasting] in PK parameters and (90% confidence interval). Low fat meal is approximately 400 kcal, 25% fat.] | AUCinf ratio | 98.6 (58.2,167.2) | -
Effect of low-fat meal (relative to fasting) [Values refer to geometric mean ratio [low-fat meal/fasting] in PK parameters and (90% confidence interval). Low fat meal is approximately 400 kcal, 25% fat.] | Cmax ratio | 115.8 (55.4, 242.1) | -
Effect of high-fat meal (relative to fasting) [Values refer to geometric mean ratio [high-fat meal/fasting] in PK parameters and (90% confidence interval). High fat meal is approximately 1000 kcal, 50% fat.] | AUCinf ratio | 115.2 (72.0, 184.5) | -
Effect of high-fat meal (relative to fasting) [Values refer to geometric mean ratio [high-fat meal/fasting] in PK parameters and (90% confidence interval). High fat meal is approximately 1000 kcal, 50% fat.] | Cmax ratio | 145.2 (77.9, 270.5) | -
Distribution
Steady state volume of distribution (L) |  | 1657
% bound to human plasma proteins |  | >98.5
Blood-to-plasma ratio |  | 0.5 to 0.7 [Values reflect the blood-to-plasma ratio of lenacapavir following a single dose intravenous administration of [^14C] lenacapavir through 336 hours postdose.]
Elimination
Apparent t1/2 |  | 10 to 12 days | 8 to 12 weeks
Clearance (L/h) |  | 3.4
% of dose of unchanged drug in plasma [Dosing in mass balance studies: single dose intravenous administration of [^14C] lenacapavir to participants.] |  | 69
Metabolism
Metabolic pathway(s) |  | CYP3A UGT1A1 (minor)
Excretion
Major routes of elimination |  | Excretion of unchanged drug into feces [Metabolized via oxidation, N-dealkylation, hydrogenation, amide hydrolysis, glucuronidation, hexose conjugation, pentose conjugation, and glutathione conjugation; via CYP3A and UGT1A1 and no single circulating metabolite accounted for >10% of plasma drug-related exposure.]
% of dose excreted in urine |  | <1
% of dose excreted in feces (% unchanged) |  | 76 (33)

Table 9. Pharmacokinetic Parameters of Lenacapavir Following Oral and Subcutaneous Administration to Adult Participants Receiving YEZTUGO
Parameter Mean (%CV) | Day 1 to end of Month 6 | Steady State
Cmax (ng/mL) | 73.8 (48.6) | 82.4 (40.4)
AUCtau (h•ng/mL) | 188108 (41.0) | 257334 (38.7)
Ctrough (ng/mL) | 27.0 (51.1) | 36.9 (53.5)
CV = coefficient of variation

Specific Populations

There were no clinically significant differences in the pharmacokinetics of lenacapavir based on age, sex assigned at birth, gender identity, ethnicity, race, body weight, severe renal impairment (creatinine clearance of 15 to less than 30 mL per minute, estimated by Cockroft-Gault method), or moderate hepatic impairment (Child-Pugh Class B). The effect of end-stage renal disease (including dialysis), or severe hepatic impairment (Child-Pugh Class C), on the pharmacokinetics of lenacapavir is unknown. As lenacapavir is greater than 98.5% protein bound, dialysis is not expected to alter exposures of lenacapavir [see Use in Specific Populations (8.6, 8.7)].

Pediatrics

The population PK parameter estimates of YEZTUGO after oral and subcutaneous administration to adolescents (weighing at least 35 kg) are provided in Table 10.

Table 10. Pharmacokinetic Parameters of Lenacapavir Following Oral and Subcutaneous Administration to Adolescent Participants Receiving YEZTUGO
Parameter Mean (%CV) | Day 1 to end of Month 6 | Steady State
Cmax (ng/mL) | 81.4 (50.8) | 90.1 (41.7)
AUCtau (h•ng/mL) | 205420 (42.1) | 279630 (39.3)
Ctrough (ng/mL) | 29.1 (51.4) | 39.8 (53.7)
CV = coefficient of variation

Pregnancy

Changes in lenacapavir exposures during pregnancy and postpartum in participants who received YEZTUGO were not considered clinically relevant compared to lenacapavir exposures observed in non-pregnant participants.

Drug Interaction Studies

Clinical Studies

A clinical drug-drug interaction study indicated that lenacapavir is a substrate of CYP3A, P-gp, and UGT1A1. Table 11 summarizes the pharmacokinetic effects of other drugs on lenacapavir.

Lenacapavir is a moderate inhibitor of CYP3A. Lenacapavir is an inhibitor of P-gp and BCRP but does not inhibit OATP. Table 12 summarizes the pharmacokinetic effects of lenacapavir on other drugs.

Table 11. Effect of Other Drugs on Lenacapavir [Single dose of lenacapavir 300 mg administered orally.]
Co-administered Drug | Dose of Co-administered Drug (mg) | Mean Ratio of Lenacapavir Pharmacokinetic Parameters (90% CI); No effect = 1.00
Co-administered Drug | Dose of Co-administered Drug (mg) | Cmax | AUC
Cobicistat (fed) (Inhibitor of CYP3A [strong] and P-gp) | 150 once daily | 2.10 (1.62, 2.72) | 2.28 (1.75, 2.96)
Darunavir / cobicistat (fed) (Inhibitor of CYP3A [strong] and inhibitor and inducer of P-gp) | 800/150 once daily | 2.30 (1.79, 2.95) | 1.94 (1.50, 2.52)
Voriconazole (fasted) (Inhibitor of CYP3A [strong]) | 400 twice daily, 200 twice daily [400 mg loading dose twice daily for a day, followed by 200 mg maintenance dose twice daily.] | 1.09 (0.81, 1.47) | 1.41 (1.10, 1.81)
Atazanavir / cobicistat (fed) (Inhibitor of CYP3A [strong], UGT1A1, and P-gp) | 300/150 once daily | 6.60 (4.99, 8.73) | 4.21 (3.19, 5.57)
Rifampin (fasted) (Inducer of CYP3A [strong], P-gp, and UGT) | 600 once daily | 0.45 (0.34, 0.60) | 0.16 (0.12, 0.20)
Efavirenz (fasted) (Inducer of CYP3A [moderate] and P-gp) | 600 once daily | 0.64 (0.45, 0.92) | 0.44 (0.32, 0.59)
Famotidine (2 hours before, fasted) | 40 once daily | 1.01 (0.75, 1.34) | 1.28 (1.00, 1.63)

Table 12. Effect of Lenacapavir on Other Drugs [Following 600 mg twice daily for 2 days, single 600 mg doses of lenacapavir were administered with each co-administered drug, resulting in lenacapavir exposures similar to or higher than those at the usual YEZTUGO dosing schedule [see Dosage and Administration (2.3)].]
Co-administered Drug | Dose of Co-administered Drug (mg) | Mean Ratio of Co-administered Drug Pharmacokinetic Parameters (90% CI) [All No Effect Boundaries are 70% to 143%.] ; No effect = 1.00
Co-administered Drug | Dose of Co-administered Drug (mg) | Cmax | AUC
Tenofovir alafenamide (fed) (substrate of P-gp) | 25 single dose | 1.24 (0.98, 1.58) | 1.32 (1.09, 1.59)
Tenofovir [Tenofovir alafenamide is converted to tenofovir in vivo.] (substrate of P-gp) |  | 1.23 (1.05, 1.44) | 1.47 (1.27, 1.71)
Pitavastatin (simultaneous administration, fed) (substrate of OATP) | 2 single dose | 1.00 (0.84, 1.19) | 1.11 (1.00, 1.25)
Pitavastatin (3 days after lenacapavir, fed) (substrate of OATP) | 2 single dose | 0.85 (0.69, 1.05) | 0.96 (0.87, 1.07)
Rosuvastatin (fed) (substrate of BCRP and OATP) | 5 single dose | 1.57 (1.38, 1.80) | 1.31 (1.19, 1.43)
Midazolam (simultaneous administration, fed) (substrate of CYP3A) | 2.5 single dose | 1.94 (1.81, 2.08) | 3.59 (3.30, 3.91)
1-hydroxymidazolam [Major active metabolite of midazolam.] (substrate of CYP3A) |  | 0.54 (0.50, 0.59) | 0.76 (0.72, 0.80)
Midazolam (1 day after lenacapavir, fed) (substrate of CYP3A) | 2.5 single dose | 2.16 (2.02, 2.30) | 4.08 (3.77, 4.41)
1-hydroxymidazolam (substrate of CYP3A) |  | 0.52 (0.48, 0.57) | 0.84 (0.80, 0.88)

In Vitro Studies

Lenacapavir is not a substrate, inducer, or inhibitor of CYP1A2, CYP2B6, CYP2C8, CYP2C9, CYP2C19, and CYP2D6. Lenacapavir is not an inducer of CYP3A.

Lenacapavir is not an inhibitor of UGT1A1.

Lenacapavir is not an inhibitor of OAT1, OAT3, OCT1, OCT2, MATE1, or MATE 2-K. Lenacapavir is not a substrate of BCRP, OATP1B1, or OATP1B3.

12.4 Microbiology

Mechanism of Action

Lenacapavir is a multistage, selective inhibitor of HIV-1 capsid function that directly binds to the interface between capsid protein (p24) subunits in hexamers. Surface plasmon resonance sensorgrams showed dose-dependent and saturable binding of lenacapavir to cross-linked wild-type capsid hexamer with an equilibrium binding constant (KD) of 1.4 nM. Lenacapavir inhibits HIV-1 replication by interfering with multiple essential steps of the viral lifecycle, including capsid-mediated nuclear uptake of HIV-1 proviral DNA (by blocking nuclear import proteins binding to capsid), virus assembly and release (by interfering with Gag/Gag-Pol functioning, reducing production of capsid protein subunits), and capsid core formation (by disrupting the rate of capsid subunit association, leading to malformed capsids).

Antiviral Activity in Cell Culture

Lenacapavir has antiviral activity that is specific to human immunodeficiency virus (HIV-1 and HIV-2). The antiviral activity of lenacapavir against laboratory and clinical isolates of HIV-1 was assessed in T-lymphoblastoid cell lines, PBMCs, primary monocyte/macrophage cells, and CD4^+ T-lymphocytes with EC50 values ranging from 30 to 190 pM. Lenacapavir displayed antiviral activity in cell culture against all HIV-1 groups (M, N, O), including subtypes A, A1, AE, AG, B, BF, C, D, E, F, G with EC50 values ranging from 20 and 160 pM. The median EC50 value for subtype B isolates (n=8) was 40 pM. Lenacapavir was 15- to 25-fold less active against HIV-2 isolates relative to HIV-1.

Resistance

In Cell Culture

HIV-1 variants with reduced susceptibility to lenacapavir have been selected in cell culture. Resistance selections with lenacapavir identified 7 substitutions in capsid: L56I, M66I, Q67H, K70N, N74D/S, and T107N singly or in dual combination that conferred 4- to >3,226-fold reduced phenotypic susceptibility to lenacapavir relative to wild-type (WT) virus. The M66I substitution alone or in combination conferred >3,226-fold decreased susceptibility to lenacapavir in a single-cycle infectivity assay; substitutions Q67H and T107N, conferred 4- to 6.3-fold decreased susceptibility; K70N, N74D and Q67H/N74S conferred 22- to 32-fold decreased susceptibility; and L56I conferred 239-fold decreased susceptibility.

In Clinical Trials

There were 2 incident infections (infections that occurred after starting YEZTUGO for HIV-1 PrEP) and 4 prevalent infections (acute infection at baseline identified after starting YEZTUGO for HIV-1 PrEP) among participants in the YEZTUGO arm of the PURPOSE 1 trial. Both incident infections occurred after the time of the primary analysis. One of the incident infections occurred in a participant after lenacapavir exposures fell below the target concentration following discontinuation of YEZTUGO, and virus from this participant had no lenacapavir resistance-associated capsid substitutions detected. The second participant with an incident infection had viral loads that were too low for genotyping. Viruses with lenacapavir resistance-associated capsid substitutions were detected in 3 of the 4 participants with prevalent infections, 2 with N74D and 1 with T107A.

There were 3 incident and 4 prevalent infections among participants in the YEZTUGO arm of the PURPOSE 2 trial. One of the incident infections occurred after the time of the primary analysis. Lenacapavir resistance-associated substitutions were detected in viruses from the 3 participants with incident infections, 2 with N74D, and 1 with Q67H/K70R. Gentoypic data were available for 3 of the 4 participants with prevalent infections. Viruses with lenacapavir resistance-associated capsid substitutions were detected in 2 of these 3 participants, both with N74D.

Cross-Resistance

The antiviral activity in cell culture of lenacapavir was determined against a broad spectrum of HIV-1 site-directed mutants and patient-derived HIV-1 isolates with resistance to the four main classes of anti-retroviral agents (INSTI, NNRTI, NRTI, and PI; n=58), as well as to viruses resistant to the gp120-directed attachment inhibitor fostemsavir, the CD4^+-directed post-attachment inhibitor ibalizumab, the CCR5 co-receptor antagonist maraviroc, and the gp41 fusion inhibitor enfuvirtide (n=42). These data indicated that lenacapavir remained fully active against all variants tested, thereby demonstrating a non-overlapping resistance profile. In addition, the antiviral activity of lenacapavir in patient isolates was unaffected by the presence of naturally occurring Gag polymorphisms and substitutions at protease cleavage sites.

13 NONCLINICAL TOXICOLOGY

13.1 Carcinogenesis, Mutagenesis, Impairment of Fertility

Carcinogenesis

Lenacapavir was not carcinogenic in a 6-month rasH2 transgenic mouse study in males or females at doses of up to 300 mg/kg/dose once every 13-weeks.

A 104-week carcinogenicity study was conducted in male and female rats at lenacapavir doses of 0, 102, 309, or 927 mg/kg by subcutaneous injection once every 13-weeks. A treatment-related increase in the incidence of malignant sarcoma at the injection site was observed in males and a treatment-related increase in combined benign fibroma and malignant fibrosarcoma at the injection site was observed in females, at the highest dose (927 mg/kg). This dose in rats resulted in an exposure approximately 44-times the human exposure at the RHD, based on AUC. These tumors are considered to be a secondary response to chronic tissue irritation and granulomatous inflammation, due to the depot effect of lenacapavir following subcutaneous injection. The clinical relevance of these findings are unknown.

Mutagenesis

Lenacapavir was not mutagenic in a battery of in vitro and in vivo genotoxicity assays, including microbial mutagenesis, chromosome aberration in human peripheral blood lymphocytes, and in in vivo rat micronucleus assays.

Impairment of Fertility

There were no effects on fertility, mating performance or early embryonic development when lenacapavir was administered to rats at systemic exposures (AUC) 8 times the exposure to humans at the RHD of YEZTUGO.

14 CLINICAL STUDIES

The efficacy and safety of YEZTUGO in reducing the risk of HIV-1 acquisition were evaluated in two randomized, double-blind, active-controlled, multinational trials (PURPOSE 1 and PURPOSE 2).

PURPOSE 1 was in cisgender adolescent girls and young women between 16 and 25 years of age in South Africa and Uganda who had unknown HIV-1 status at screening and who were at risk of acquiring HIV-1 based on sexual activity with male partners. Participants who tested negative for HIV-1 at screening and baseline were randomized to receive YEZTUGO (N=2134), once daily DESCOVY (N=2136), or once daily TRUVADA (N=1068) in a 2:2:1 ratio.

PURPOSE 2 was in cisgender men, transgender women, transgender men, and gender nonbinary individuals 16 years of age and older who had unknown HIV-1 status at screening and who were at risk of acquiring HIV-1 based on sexual activity with male partners. PURPOSE 2 enrolled participants in Argentina, Brazil, Mexico, Peru, South Africa, Thailand, and the United States. Participants who tested negative for HIV-1 at screening and baseline were randomized to receive YEZTUGO (N=2179) or once daily TRUVADA (N=1086) in a 2:1 ratio.

PURPOSE 1

In PURPOSE 1, the median age of participants was 21 years (range, 16-26); and 99.9% were Black. Baseline characteristics in the randomized participants were similar to the screened population. Over 99% of YEZTUGO injections were administered into the abdomen and each dose was administered in two locations. A total of 32 pregnant participants received YEZTUGO injections into the thigh and each dose was administered bilaterally (i.e., one injection in the right thigh and one injection in the left thigh).

The efficacy endpoint was the rate of incident HIV-1 infections per 100 person-years in participants randomized to YEZTUGO compared with the rate of incident HIV-1 infections per 100 person-years in participants randomized to TRUVADA. YEZTUGO demonstrated superiority with a 100% reduction in the risk of incident HIV-1 infection over TRUVADA (Table 13).

Table 13. Overall HIV-1 Infection Outcomes in PURPOSE 1 [The determination of efficacy was based on planned interim analyses (which became the final analyses) following sequential testing of HIV-1 incidence for YEZTUGO compared to background followed by YEZTUGO compared to TRUVADA, all at alpha level of 0.0026 when 50% of randomized participants completed at least 52 weeks of follow-up or prematurely discontinued from the study. YEZTUGO also demonstrated superiority in the risk of incident HIV-1 infection over background HIV-1 incidence.]
 | YEZTUGO N=2134 | TRUVADA N=1068 | Rate Ratio (95% CI)
Person-years | 1939 | 949 | -
HIV-1 infections (incidence rate per 100 person-years) | 0 (0.00) | 16 (1.69) | YEZTUGO / TRUVADA: 0.000 (0.000, 0.101) p <0.0001
CI = confidence interval

PURPOSE 2

In PURPOSE 2, the median age of participants was 29 years (range, 17-74); 67% were non White; 63% were Hispanic/Latine; and 22% identified as gender-diverse (transgender women, transgender men, and gender nonbinary people). Baseline characteristics in the randomized participants were similar to the screened population. YEZTUGO injections were administered into the abdomen and each dose was administered in two locations.

The efficacy endpoint was the rate of incident HIV-1 infections per 100 person-years in participants randomized to YEZTUGO compared with the rate of incident HIV-1 infections per 100 person-years in participants randomized to TRUVADA. YEZTUGO demonstrated superiority with an 89% reduction in the risk of incident HIV-1 infection over TRUVADA (Table 14).

Table 14. Overall HIV-1 Infection Outcomes in PURPOSE 2 [The determination of efficacy was based on planned interim analyses (which became the final analyses) following sequential testing of HIV-1 incidence for YEZTUGO compared to background followed by YEZTUGO compared to TRUVADA, all at alpha level of 0.0026 when 50% of randomized participants completed at least 52 weeks of follow-up or prematurely discontinued from the study. YEZTUGO also demonstrated superiority in the risk of incident HIV-1 infection over background HIV-1 incidence.]
 | YEZTUGO N=2179 | TRUVADA N=1086 | Rate Ratio (95% CI)
Person-years | 1938 | 967 | -
HIV-1 infections (incidence rate per 100 person-years) | 2 (0.1) | 9 (0.93) | YEZTUGO / TRUVADA: 0.111 (0.024, 0.513) p = 0.00245
CI = confidence interval

16 HOW SUPPLIED/STORAGE AND HANDLING

YEZTUGO tablets, 300 mg are beige, capsule-shaped, and film-coated with “GSI” debossed on one side and “62L” on the other side.

Each YEZTUGO bottle contains 4 tablets (NDC 61958-3401-1), a silica gel desiccant, polyester coil, and is closed with a child resistant closure. Do not remove the desiccant packet.

Keep bottle tightly closed.

Store bottle at 20 °C – 25 °C (68 °F – 77 °F), excursions permitted to 15 °C – 30 °C (59 °F – 86 °F) (see USP Controlled Room Temperature).

Dispense and store only in original container.

YEZTUGO injection is packaged in a dosing kit (NDC 61958-3402-1) containing:

- 2 single-dose clear glass vials, each containing sufficient volume to allow withdrawal of 463.5 mg/1.5 mL (309 mg/mL) of lenacapavir. The injection solution is sterile, preservative-free, clear, and yellow with no visible particles. Vials are sealed with a stopper and aluminum overseal with flip-off cap.
- 2 disposable syringes, 2 withdrawal needles (18-gauge, 1½ inch), and 2 injection safety needles for subcutaneous injection (22-gauge, ½ inch).

The vial stoppers are not made with natural rubber latex.

Store at 20 °C – 25 °C (68 °F – 77 °F), excursions permitted to 15 °C – 30 °C (59 °F – 86 °F).

Keep the vials in the original carton until just prior to preparation of the injections in order to protect from light.

Once the solution has been drawn into the syringes, the injections should be administered as soon as possible.

Discard any unused portion of the solution.

17 PATIENT COUNSELING INFORMATION

Advise the individual to read the FDA-approved patient labeling (Patient Information).

Important Information for Individuals Receiving YEZTUGO for HIV-1 PrEP

Advise individuals about the following [see Warnings and Precautions (5.1)]:

- YEZTUGO should be used for PrEP as part of an overall HIV-1 prevention strategy, including adherence to the administration schedule and safer sex practices, including condoms, to reduce the risk of STIs.
- YEZTUGO is not always effective in preventing HIV-1 acquisition [see Clinical Studies (14)]. The time from initiation of YEZTUGO for HIV-1 PrEP to maximal protection against HIV-1 infection is unknown.
- Counsel individuals on the use of other prevention measures (e.g., knowledge of partner HIV-1 status, testing for STIs, condom use). Inform individuals about and support their efforts in reducing sexual behaviors associated with HIV-1 acquisition risk.
- YEZTUGO should be used to reduce the risk of HIV-1 acquisition only in individuals confirmed to be HIV-1 negative. Individuals must have a negative HIV-1 test prior to initiating YEZTUGO, prior to each subsequent injection of YEZTUGO, and additionally as clinically appropriate, with a test approved or cleared by the FDA as an aid in the diagnosis of acute or primary HIV-1 infection [see Dosage and Administration (2.1), Contraindications (4), and Warnings and Precautions (5.1, 5.2)].
- Counsel and support individuals on adhering to the required initiation and continuation dosing schedule, on the use of other measures to reduce the risk of STIs, and on the importance of testing for HIV-1 and other STIs.
- Some individuals, such as adolescents, may benefit from additional counseling and appointment reminders to support adherence.

Risk of Resistance

Advise individuals that there is a risk of developing resistance to YEZTUGO if HIV-1 is acquired either before or when receiving YEZTUGO, or following discontinuation of YEZTUGO. HIV-1 resistance substitutions may emerge in individuals with undiagnosed HIV-1 infection who are taking only YEZTUGO, because YEZTUGO alone does not constitute a complete regimen for HIV-1 treatment [see Warnings and Precautions (5.2)]. Inform individuals that YEZTUGO can remain in the body for up to 12 months or longer after receiving their last injection [see Warnings and Precautions (5.3)].

To minimize this risk, it is essential that individuals are routinely tested to confirm HIV-1 negative status. Advise individuals that if they are confirmed to have HIV-1, they must immediately be transitioned to a complete HIV-1 treatment regimen [see Warnings and Precautions (5.2)].

Inform individuals that alternative forms of PrEP should be considered and initiated within 28 weeks of the last YEZTUGO injection [see Warnings and Precautions (5.2)].

Anticipated Delayed Injections

Advise individuals to contact their healthcare provider if the scheduled 6-month injection is anticipated to be delayed by more than 2 weeks. Advise that YEZTUGO tablets may be taken for up to 6 months, if needed, until injections resume. Advise individuals that oral dosing should be used on an interim basis only and that the continuation injection dosage should be resumed at the earliest possible opportunity [see Dosage and Administration (2.4)].

Injection Site Reactions

Inform individuals that a subcutaneous drug depot forms following YEZTUGO injection. Advise that, in some individuals, this may lead to a nodule at the injection site [see Adverse Reactions (6.1) and Clinical Pharmacology (12.3)].

Drug Interactions

YEZTUGO may interact with certain drugs; therefore, advise individuals to report to their healthcare provider the use of any other prescription or non-prescription medication or herbal products [see Drug Interactions (7)].

If YEZTUGO is discontinued, advise individuals that YEZTUGO may remain in the body and affect certain other drugs for up to 9 months after receiving their last injection [see Drug Interactions (7.2)].

Pregnancy Registry

Inform individuals that there is an antiretroviral pregnancy registry to monitor fetal outcomes of pregnant individuals exposed to YEZTUGO [see Use in Specific Populations (8.1)].

YEZTUGO, DESCOVY, and TRUVADA are trademarks of Gilead Sciences, Inc., or its related companies. All other trademarks referenced herein are the property of their respective owners.

Manufactured for:
Gilead Sciences, Inc.
333 Lakeside Dr.
Foster City, CA 94404.

© 2025 Gilead Sciences, Inc. All rights reserved.

PATIENT INFORMATION

YEZTUGO® (yez-TOO-go)
(lenacapavir)
tablets, for oral use

YEZTUGO® (yez-TOO-go)
(lenacapavir)
injection, for subcutaneous use

What is the most important information I should know about YEZTUGO?
Important information for people who receive YEZTUGO to reduce their risk of getting human immunodeficiency virus-1 (HIV-1), also called pre-exposure prophylaxis or “PrEP”:
Before receiving YEZTUGO to reduce your risk of getting HIV-1:

- You must be HIV-1 negative to start YEZTUGO. You must get tested to make sure that you do not already have HIV-1.
- Do not receive YEZTUGO unless you are confirmed to be HIV-1 negative.
- Some HIV-1 tests can miss HIV-1 infection in a person who has recently acquired HIV-1. If you have flu-like symptoms, you could have recently acquired HIV-1. Tell your healthcare provider if you had a flu-like illness within the last month before starting YEZTUGO or at any time while receiving YEZTUGO. Symptoms of a new HIV-1 infection include:

- tiredness
- joint or muscle aches
- sore throat
- rash
- enlarged lymph nodes in the neck or groin

- fever
- headache
- vomiting or diarrhea
- night sweats

While you are receiving YEZTUGO:

- YEZTUGO does not prevent other sexually transmitted infections (STIs).
  - Practice safer sex by using a latex or polyurethane condom to reduce the risk of getting STIs.
  - Get tested for other STIs such as syphilis, chlamydia, and gonorrhea.
- You must stay HIV-1 negative to keep receiving YEZTUGO.
  - Know your HIV-1 status and the HIV-1 status of your partners.
  - Ask your partners with HIV-1 if they are taking anti-HIV-1 medicine and have an undetectable viral load. An undetectable viral load is when the amount of virus in the blood is too low to be measured in a lab test. To maintain an undetectable viral load, your partners must keep taking HIV-1 medicine as prescribed. Your risk of getting HIV-1 is lower if your partners with HIV-1 are taking effective treatment.
  - Get tested for HIV-1 with each YEZTUGO injection or when your healthcare provider tells you. You should not miss any HIV-1 tests. If you get HIV-1 and continue receiving YEZTUGO because you do not know you have HIV-1, the HIV-1 may become harder to treat.
  - If you think you were exposed to HIV-1, tell your healthcare provider right away. They may want to do more tests to be sure you do not have HIV-1.
  - Get information and support to help reduce sexual behaviors associated with the risk of getting HIV-1.
  - Follow the YEZTUGO dosing schedule, which includes returning to a healthcare provider for your scheduled injections every 6 months. Missing YEZTUGO injections or tablets increases your risk of getting HIV-1 (see “How should I receive YEZTUGO”).

- If you get HIV-1, you will need to immediately take other medicines to treat HIV-1. YEZTUGO is not approved for treatment of HIV-1.

If you have HIV-1 and receive only YEZTUGO, over time your HIV-1 may become harder to treat.

What is YEZTUGO?
YEZTUGO is a prescription medicine that is used for HIV-1 PrEP to reduce the risk of getting HIV-1 in adults and adolescents who weigh at least 77 pounds (at least 35 kg).
HIV-1 is the virus that causes Acquired Immune Deficiency Syndrome (AIDS).
It is not known if YEZTUGO is safe and effective in children weighing less than 77 pounds (less than 35 kg).

Do not receive YEZTUGO if you:

- already have HIV-1. If you already have HIV-1, you will need to take other medicines to treat HIV-1. YEZTUGO is not approved for treatment of HIV-1.
- do not know your HIV-1 status. You may already have HIV-1. If you have HIV-1, you will need to take other medicines to treat it. YEZTUGO can only help reduce your risk of getting HIV-1 before you get it.

What should I tell my healthcare provider before receiving YEZTUGO?
Before receiving YEZTUGO, tell your healthcare provider about all your medical conditions, including if you:

- are pregnant or plan to become pregnant. Tell your healthcare provider if you become pregnant while or after receiving YEZTUGO.
  Pregnancy Registry: There is a pregnancy registry for individuals who receive YEZTUGO during pregnancy. The purpose of this registry is to collect information about the health of you and your baby. Talk with your healthcare provider about how you can take part in this registry.
- are breastfeeding or plan to breastfeed. A small amount of YEZTUGO is present in breast milk. Talk to your healthcare provider about the best way to feed your baby while you are receiving YEZTUGO.

Tell your healthcare provider about all the medicines you take, including prescription and over-the-counter medicines, vitamins, and herbal supplements.
Some medicines may interact with YEZTUGO. Keep a list of your medicines and show it to your healthcare provider and pharmacist when you get a new medicine.

- You can ask your healthcare provider or pharmacist for a list of medicines that interact with YEZTUGO.
- Do not start a new medicine without telling your healthcare provider. Your healthcare provider can tell you if it is safe to receive YEZTUGO with other medicines.
- YEZTUGO may affect certain other medicines for up to 9 months after your last injection.

How will I receive and take YEZTUGO?

- YEZTUGO consists of injections and tablets.
  - YEZTUGO injections will be given to you by a healthcare provider under the skin (subcutaneous injection). The injection can be given in your stomach-area (abdomen) or upper leg (thigh).
  - Take YEZTUGO tablets by mouth, with or without food.
- Your dosing schedule will start as follows:
  - On Day 1, you will receive 2 YEZTUGO injections and take 2 YEZTUGO tablets.
  - On Day 2, you will take 2 YEZTUGO tablets.
- After completing the start of your dosing schedule, you will receive 2 YEZTUGO injections every 6 months (26 weeks) from the date of your last injection.
- Stay under the care of a healthcare provider while receiving YEZTUGO. It is important that you attend your scheduled appointments to receive your injections of YEZTUGO.
- If you miss taking your tablets on Day 2, take them as soon as possible. Your Day 1 and Day 2 tablets should not be taken on the same day.
- If you miss or need to delay your scheduled every 6 months injection of YEZTUGO by more than 2 weeks, call your healthcare provider right away to discuss your PrEP options.
  - If you need to delay your scheduled YEZTUGO injection appointment, there is the option to temporarily take YEZTUGO tablets. You will take 1 YEZTUGO tablet by mouth 1 time every 7 days, until your injections resume.
  - It is important to continue receiving YEZTUGO as scheduled. Missing YEZTUGO injections or tablets may increase your risk of getting HIV-1.
- If you stop receiving YEZTUGO, talk to your healthcare provider about other options to reduce the risk of getting HIV-1.
- If you take too many YEZTUGO tablets, call your healthcare provider or go to the nearest hospital emergency room right away.

What are the possible side effects of YEZTUGO?
The most common side effects of YEZTUGO are injection site reactions, headache, and nausea.
Injection site reactions are common side effects experienced by most people who take YEZTUGO. These reactions where you receive the injection may include a lump or bump, pain, skin hardening, swelling, itching, redness, bruising, or warmth. If you develop a lump or hardened skin at the injection site, it may be felt but not seen and may take longer to go away than other injection site reactions.
Rarely, improper injection of YEZTUGO by a healthcare provider can lead to serious injection site reactions like severe skin damage (necrosis) or open sores (ulcer). Tell your healthcare provider if you have any injection site reactions or other side effects.
These are not all of the possible side effects of YEZTUGO.
Call your doctor for medical advice about side effects. You may report side effects to FDA at 1-800-FDA-1088.

How should I store YEZTUGO tablets?

- Store YEZTUGO tablets at room temperature between 68 °F to 77 °F (20 °C to 25 °C).
- YEZTUGO bottle contains a desiccant packet to help keep your medicine dry (protect it from moisture). Keep the desiccant packet in the bottle. Do not eat the desiccant packet.
- Keep YEZTUGO tablets in their original bottle.
- Keep the bottle tightly closed.
- YEZTUGO bottle has a child resistant cap closure.

Keep YEZTUGO and all medicines out of reach of children.

General information about the safe and effective use of YEZTUGO.
Medicines are sometimes prescribed for purposes other than those listed in a Patient Information leaflet. Do not use YEZTUGO for a condition for which it was not prescribed. Do not give YEZTUGO to other people. It may harm them. You can ask your pharmacist or healthcare provider for information about YEZTUGO that is written for health professionals.

What are the ingredients in YEZTUGO?
Active ingredient: lenacapavir sodium
Inactive ingredients:
YEZTUGO tablets: copovidone, croscarmellose sodium, magnesium stearate, mannitol, microcrystalline cellulose, and poloxamer 407. The tablets are film-coated with a coating material containing iron oxide black, iron oxide red, iron oxide yellow, polyethylene glycol, polyvinyl alcohol, talc, and titanium dioxide.
YEZTUGO injection: polyethylene glycol 300 and water for injection.
Manufactured and distributed by: Gilead Sciences, Inc. Foster City, CA 94404
YEZTUGO is a trademark of Gilead Sciences, Inc., or its related companies. All other trademarks referenced herein are the property of their respective owners.
© 2025 Gilead Sciences, Inc. All rights reserved. 220018-GS-000/IFU-WD-000
For more information, call 1-800-445-3235 or go to www.YEZTUGO.com.

This Patient Information has been approved by the U.S. Food and Drug Administration.

Issued: 6/2025

PRINCIPAL DISPLAY PANEL - 4 Tablet Bottle Label

NDC 61958-3401-1
4 tablets

Yeztugo®
(lenacapavir) tablets
300 mg per tablet

Talk to your healthcare provider
before taking Yeztugo tablets.

Your healthcare provider will tell you
when to take Yeztugo tablets.

GILEAD
© 2025 Gilead Sciences, Inc.

PRINCIPAL DISPLAY PANEL - Kit Carton

Rx only
NDC 61958-3402-1

Yeztugo®
(lenacapavir) injection

463.5 mg/1.5 mL (309 mg/mL)

For Subcutaneous Injection

Contents

- 2 x 1.5 mL lenacapavir single-dose vials
- 2 withdrawal needles (18 gauge, 1½ inch)
- 2 syringes
- 2 injection needles (22 gauge, ½ inch)
- Prescribing Information
- Instructions for Use
- Patient Information

Both 463.5 mg/1.5 mL (2 single-dose vials) must be
administered to receive the 927 mg dose.

For Healthcare Professional administration only.

GILEAD